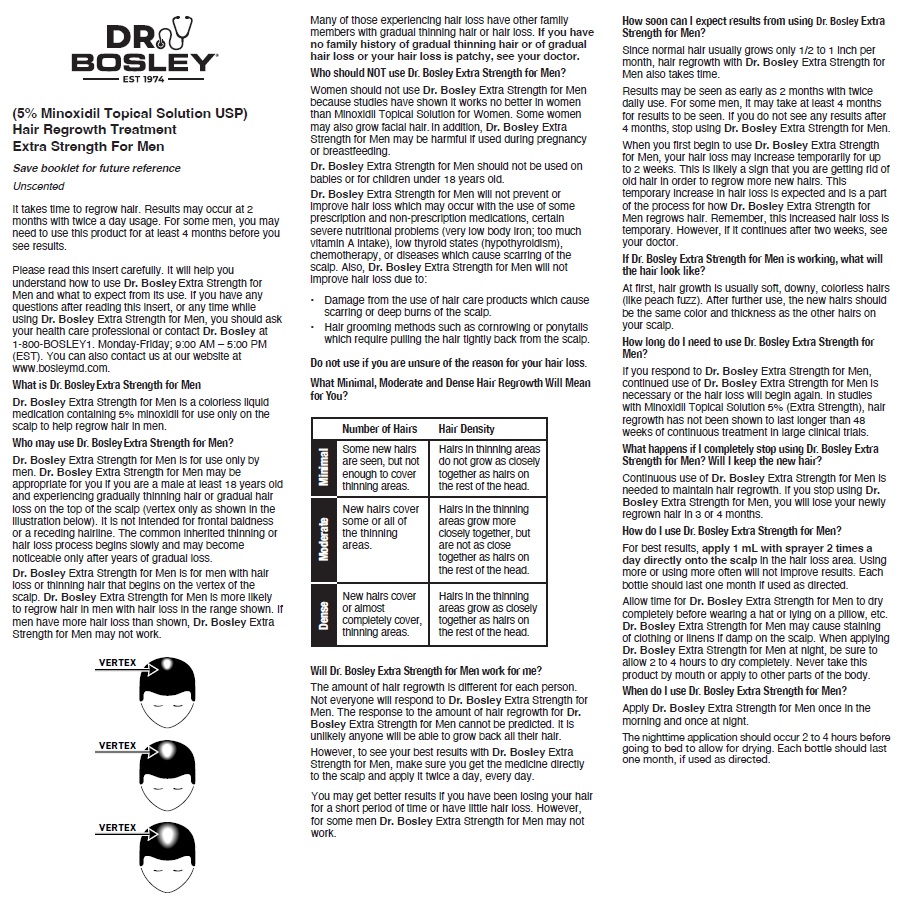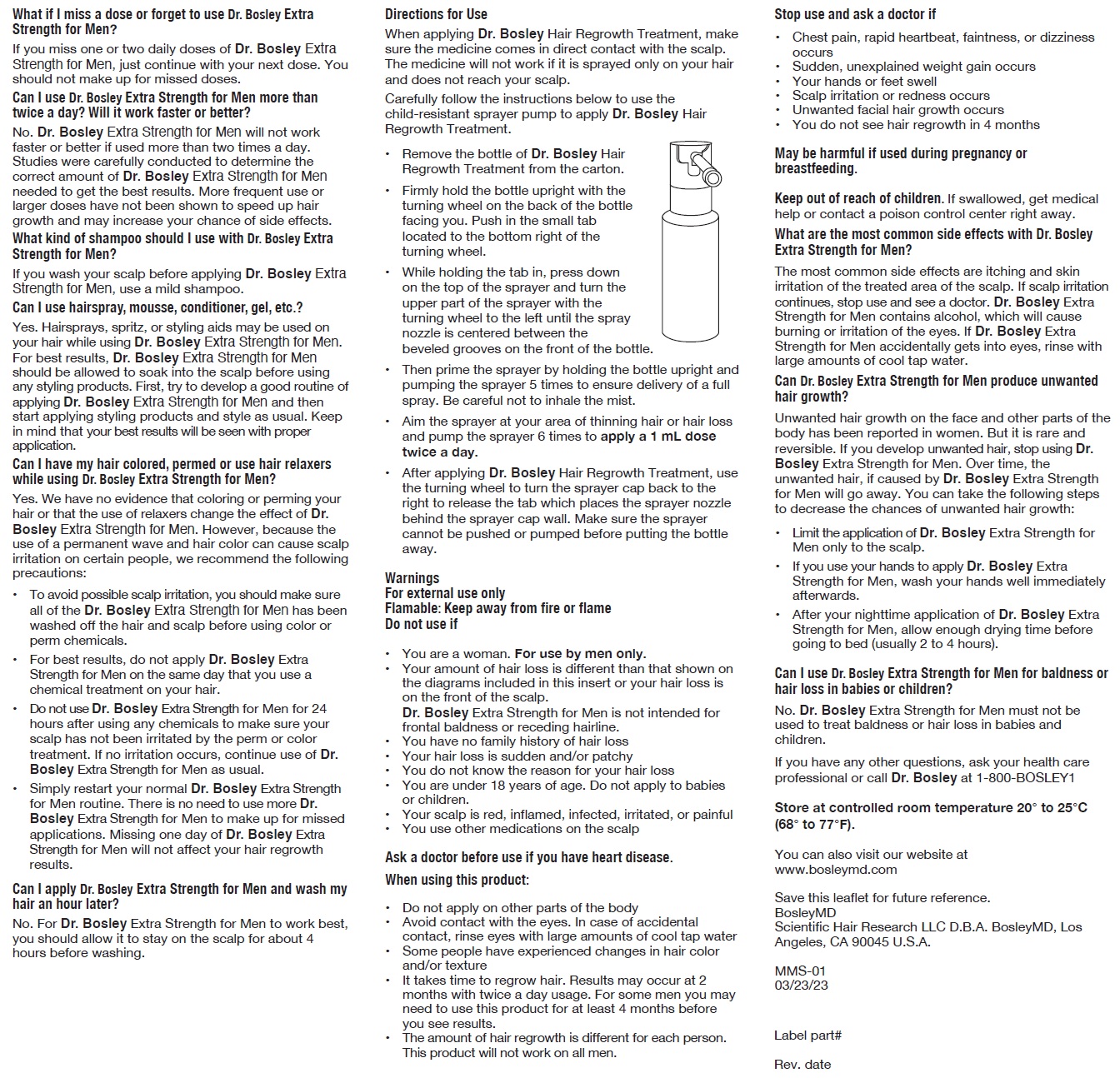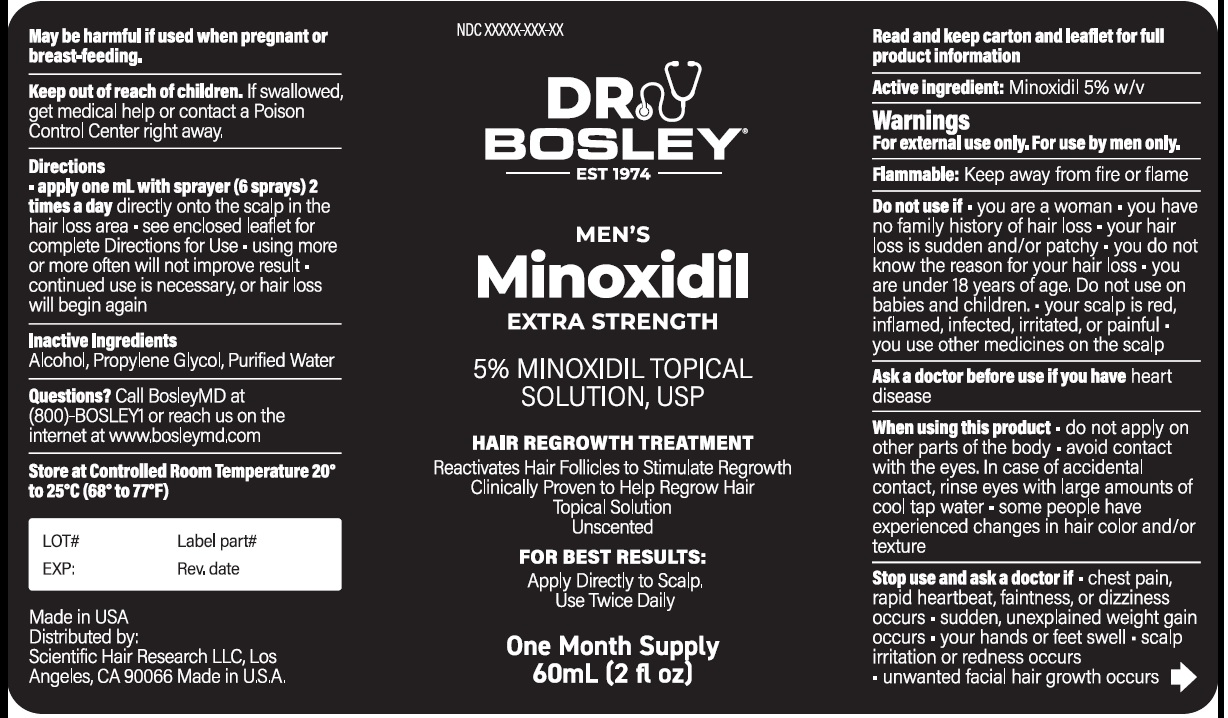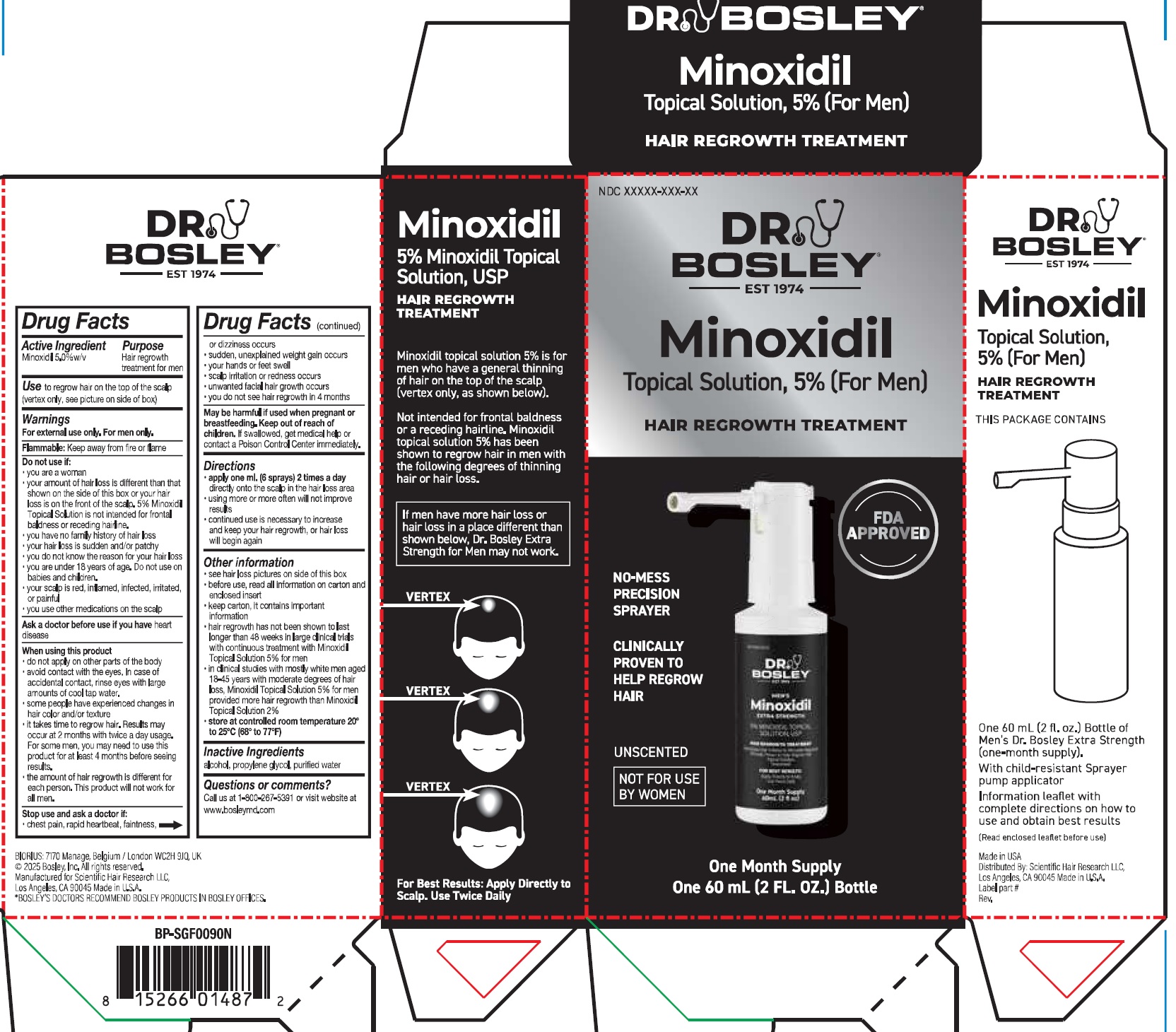 DRUG LABEL: Dr. Bosley Minoxidil (For Men) Hair Regrowth Treatment
NDC: 69113-913 | Form: SOLUTION
Manufacturer: Scientific Hair Research, LLC
Category: otc | Type: HUMAN OTC DRUG LABEL
Date: 20251209

ACTIVE INGREDIENTS: MINOXIDIL 50 mg/1 mL
INACTIVE INGREDIENTS: ALCOHOL; PROPYLENE GLYCOL; WATER

Dr. Bosley Minoxidil Topical Solution 5% (For Men) Hair Regrowth Treatment

Active Ingredient

Minoxidil 5.0%w/v

Purpose

Hair regrowth treatment for men

Use

to regrow hair on the top of the scalp (vertex only, see picture on side of box)

Warnings

For external use only. For men only.
Flammable:Keep away from fire or flame

Do not use if:

- you are a woman
- your amount of hair loss is different than that shown on the side of this box or your hair loss is on the front of the scalp. 5% Minoxidil Topical Solution is not intended for frontal baldness or receding hairline.
- you have no family history of hair loss
- your hair loss is sudden and/or patchy
- you do not know the reason for your hair loss
- you are under 18 years of age. Do not use on babies and children.
- your scalp is red, inflamed, infected, irritated, or painful
- you use other medications on the scalp

Ask a doctor before use if you have

heart disease

When using this product

- do not apply on other parts of the body
- avoid contact with the eyes. In case of accidental contact, rinse eyes with large amounts of cool tap water.
- some people have experienced changes in hair color and/or texture
- it takes time to regrow hair. Results may occur at 2 months with twice a day usage. For some men, you may need to use this product for at least 4 months before seeing results.
- the amount of hair regrowth is different for each person. This product will not work for all men.

Stop use and ask a doctor if:

- chest pain, rapid heartbeat, faintness, or dizziness occurs
- sudden, unexplained weight gain occurs
- your hands or feet swell
- scalp irritation or redness occurs
- unwanted facial hair growth occurs
- you do not see hair regrowth in 4 months
- May be harmful if used when pregnant or breastfeeding.

Keep out of reach of children.

If swallowed, get medical help or contact a Poison Control Center immediately.

Directions

- apply one ml. (6 sprays) 2 times a day directly onto the scalp in the hair loss area
- using more or more often will not improve results
- continued use is necessary to increase and keep your hair regrowth, or hair loss will begin again

Other information

- see hair loss picture on side of this box
- before use, read all information on carton and enclosed insert
- keep carton, it contains important information
- hair regrowth has not been shown to last longer than 48 weeks in large clinical trials with continuous traetment with Minoxidil Topical Solution 5 % for men
- in clinical studies with mostly white men aged 18-45 years with moderate degrees of hair loss, Minoxidil Topical Solution 5% for men provided more hair regrowth than Minoxidil Topical Solution 2 %
- store at controlled room temperature 20° to 25°C (68° to 77°F)

Inactive Ingredients

alcohol, propylene glycol, purified water

Question or comments?

Call us at 1-800-267-5391 or visit website at www.bosleymd.com